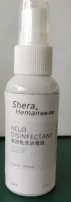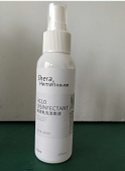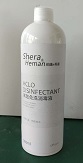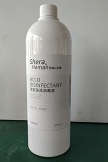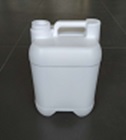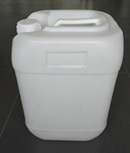 DRUG LABEL: Disinfectant
NDC: 74457-001 | Form: LIQUID
Manufacturer: Shera Heman Zhejiang Biotechnologies Co.,Ltd.
Category: otc | Type: HUMAN OTC DRUG LABEL
Date: 20200407

ACTIVE INGREDIENTS: HYPOCHLOROUS ACID 0.1 mg/1 mL
INACTIVE INGREDIENTS: WATER

Disinfectant

HYPOCHLOROUS ACID 0.01% v/v

Water

ACTIVE INGREDIENT

HYPOCHLOROUS ACID 0.01% v/v

PURPOSE

Products used to kill bacteria and viruses, prevent disease, and suppress spread

INDICATIONS AND USAGE

Sterilize by spraying on objects or skin surface

WARNINGS

For external use only.

DO NOT USE

in children less than 2 months of age
on open skin wounds

When using this product keep out of eyes, ears, and mouth. In case of contact with eyes, rinse eyes thoroughly with water.
Stop use and ask a doctor if irritation or rash occurs. These may be signs of a serious condition.
Keep out of reach of children. If swallowed, get medical help or contact a Poison Control Center right away.

Stop use and ask a doctor if irritation or rash occurs. These may be signs of a serious condition.

Keep out of reach of children. If swallowed, get medical help or contact a Poison Control Center right away.

DOSAGE AND ADMINISTRATION

Spray on the surface of objects or human skin

Supervise children under 6 years of age when using this product to avoid swallowing.

STORAGE AND HANDLING

Store between 15-30C (59-86F)
Avoid freezing and excessive heat above 40C (104F)

INACTIVE INGREDIENT

water

PACKAGE LABEL

50mL NDC: 74457-001-01

100mL NDC: 74457-002-01

300mL NDC: 74457-003-01

500mL NDC: 74457-004-01

1000mL NDC: 74457-005-01

4L NDC: 74457-006-01

25L NDC: 74457-007-01